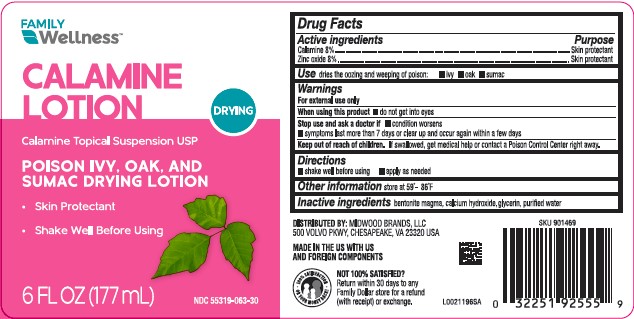 DRUG LABEL: Calamine
NDC: 55319-063 | Form: LOTION
Manufacturer: Family Dollar Stores, Inc
Category: otc | Type: HUMAN OTC DRUG LABEL
Date: 20260224

ACTIVE INGREDIENTS: FERRIC OXIDE RED 80 mg/1 mL; ZINC OXIDE 80 mg/1 mL
INACTIVE INGREDIENTS: BENTONITE; CALCIUM HYDROXIDE; GLYCERIN; WATER

Family Wellness 063.001/063AA
Calamine Lotion

Active ingredients

Calamine 8%
Zinc oxide 8%

Purpose

Skin Protectant

Use

dries the oozing and weeping of poison:

- ivy
- oak
- sumac

Warnings

For external use only

When using this product

do not get into eyes

Stop use and ask a doctor if

- condition worsens
- symptoms last more than 7 days or clear up and occur again within a few days

Keep out of reach of children.

If swallowed, get medical help or contact a Poison Control Center right away.

Directions

- shake well before using
- apply as needed

Other information

store at 59⁰ - 86⁰F

Inactive ingredients

bentonite magma, calcium hydroxide, glycerin, purified water

ADVERSE REACTION

DISTRIBUTED BY: MIDWOOD BRANDS, LLC

500 VOLVO PKWY, CHESAPEAKE,VA 23320 USA

MADE IN THE US WITH US AND FOREIGN COMPONENTS

100% SATISFACTION OR YOUR MONEY BACK!

NOT 100% SATISFIED?

Return within 30 days to any Family Dollar store for a refund (with receipt) or exchange.

Principal display panel

FAMILY Wellness™

CALAMINE LOTION

DRYING

Calamine Topical Suspension USP

POISON IVY, OAK, AND SUMAC DRYING LOTION

- Skin Protectant
- Shake Well Before Using

6 FL OZ (177 mL)

NDC 55319-063-30